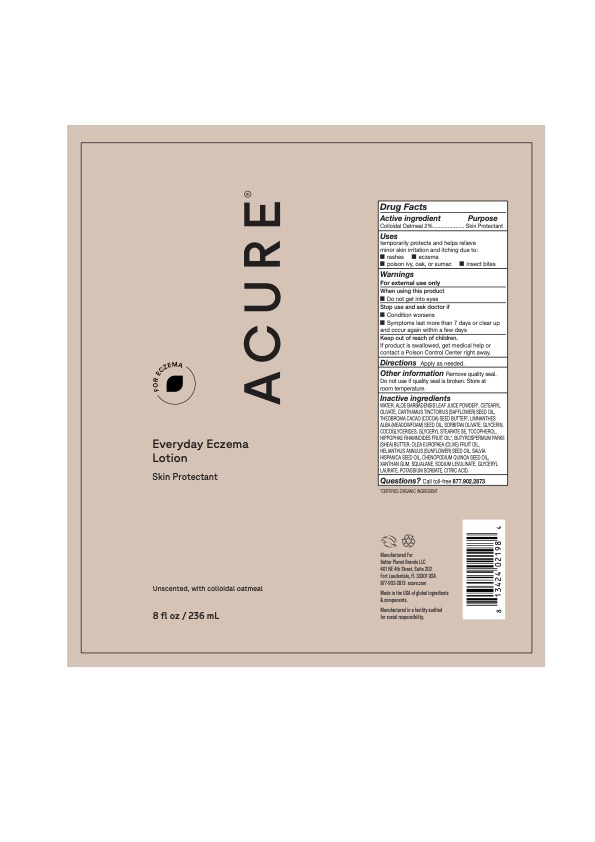 DRUG LABEL: Everyday Eczema
NDC: 54136-181 | Form: LOTION
Manufacturer: Better Planet Brands LLC
Category: otc | Type: HUMAN OTC DRUG LABEL
Date: 20251203

ACTIVE INGREDIENTS: OATMEAL 2 g/100 g
INACTIVE INGREDIENTS: SUNFLOWER OIL; SAFFLOWER OIL; SQUALANE; MEADOWFOAM SEED OIL; SODIUM LEVULINATE; XANTHAN GUM; COCOA BUTTER; SORBITAN OLIVATE; TOCOPHEROL; OLIVE OIL; COCO-GLYCERIDES; LAVENDER OIL; ANHYDROUS CITRIC ACID; ALOE VERA LEAF; GLYCERYL LAURATE; POTASSIUM SORBATE; HIPPOPHAE RHAMNOIDES SEED OIL; GLYCERYL STEARATE SE; CETEARYL OLIVATE; WATER; GLYCERIN

Everyday Eczema Lotion, Oxygen

Active Ingredients

Colloidal Oatmeal 2.0%

Purpose

Skin Protectant

Uses

temporarily protects and helps relieve minor skin irritation and itching due to:

• rashes • eczema poison ivy, oak, or sumac

• insect bites

Warnings

For external use only

When using this product

• Do not get into eyes

When using this product

• Do not get into eyes

Stop use and ask doctor if

Condition worsens
Symptoms last more than 7 days or clear up and occur again within a few

Keep out of reach of children.

If product is swallowed, get medical help or contact a Poison Control Center right away.

Directions

Apply as needed.

Other information

Remove quality seal.

Do not use if quality seal is broken. Store at room temperature.

Inactive ingredients

WATER, ALOE BARBADENSIS LEAF JUICE POWDER*, CARTHAMUS TINCTORIUS (SAFFLOWER) SEED OIL, COCOGLYCERIDES, GLYCERYL STEARATE SE, CETEARYL OLIVATE, THEOBROMA CACAO (COCOA) SEED BUTTER*, LIMNANTHES ALBA (MEADOWFOAM) SEED OIL, GLYCERIN, SORBITAN OLIVATE, HELIANTHUS ANNUUS (SUNFLOWER) SEED OIL", TOCOPHEROL, LAVANDULA ANGUSTIFOLIA (LAVENDER) OIL, HIPPOPHAE RHAMNOIDES FRUIT OIL*, OLEA EUROPAEA (OLIVE) FRUIT OIL, XANTHAN GUM, SQUALANE, SODIUM LEVULINATE, GLYCERYL LAURATE, POTASSIUM SORBATE, CITRIC ACID.

Questions?

Call toll-free 877.902.2873